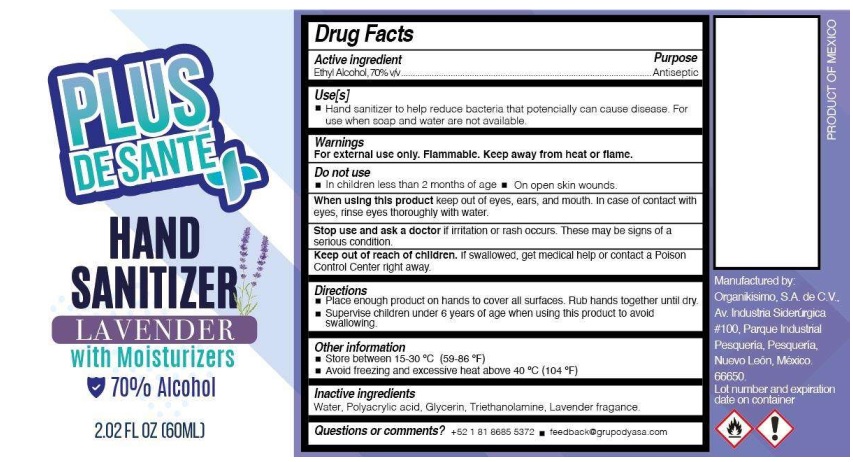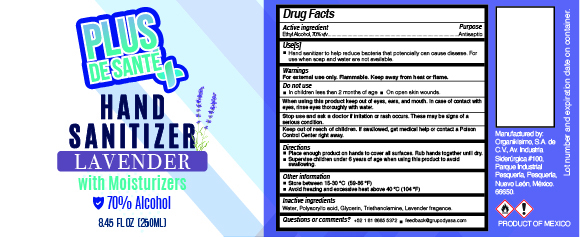 DRUG LABEL: Hand Sanitizer
NDC: 79337-161 | Form: GEL
Manufacturer: Organikisimo, S.A. de C:V.
Category: otc | Type: HUMAN OTC DRUG LABEL
Date: 20200921

ACTIVE INGREDIENTS: ALCOHOL 70 mL/100 mL
INACTIVE INGREDIENTS: TROLAMINE 0.1 mL/100 mL; GLYCERIN 0.8 mL/100 mL; WATER 28.3 mL/100 mL; POLYACRYLIC ACID (8000 MW) 0.6 mL/100 mL; FRAGRANCE LAVENDER & CHIA F-153480 0.2 mL/100 mL

7337-161-01 ORG-250 ML LAVENDER GEL NDC 7337-161-01

Active Ingredient(s)

Ethyl Alcohol 70% v/v. Purpose: Antiseptic

Purpose

Antiseptic, Hand Sanitizer

Use

Hand Sanitizer to help reduce bacteria that potentially can cause disease. For use when soap and water are not available.

Warnings

For external use only. Flammable. Keep away from heat or flame

Do not use

- in children less than 2 months of age
- on open skin wounds

When using this product keep out of eyes, ears, and mouth. In case of contact with eyes, rinse eyes thoroughly with water.
Stop use and ask a doctor if irritation or rash occurs. These may be signs of a serious condition.
Keep out of reach of children. If swallowed, get medical help or contact a Poison Control Center right away.

Stop use and ask a doctor if irritation or rash occurs. These may be signs of a serious condition.

Keep out of reach of children. If swallowed, get medical help or contact a Poison Control Center right away.

Directions

- Place enough product on hands to cover all surfaces. Rub hands together until dry.
- Supervise children under 6 years of age when using this product to avoid swallowing.

Other information

- Store between 15-30C (59-86F)
- Avoid freezing and excessive heat above 40C (104F)

Inactive ingredients

Water, Polyacylic acid, glycerin,Triethanolamine,lavender Fragrance.

Package Label - Principal Display Panel

250 ml NDC:79337-161-01

Lavender 60mL

60 mL NDC: 79337-161-02